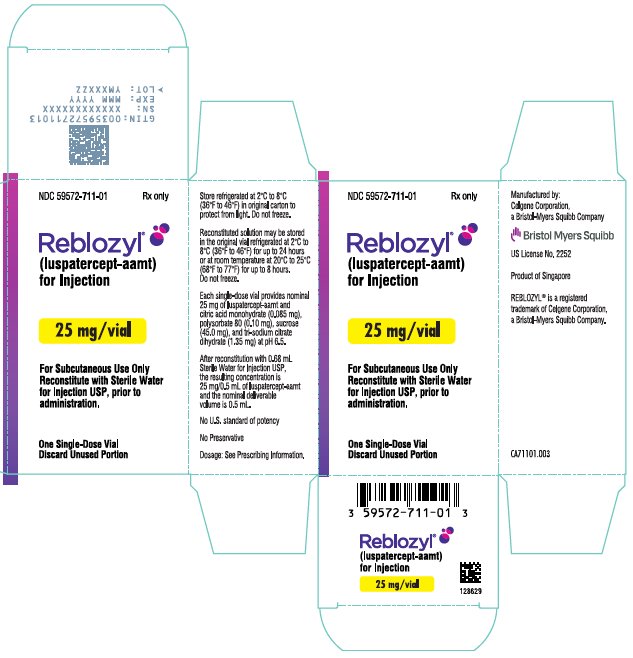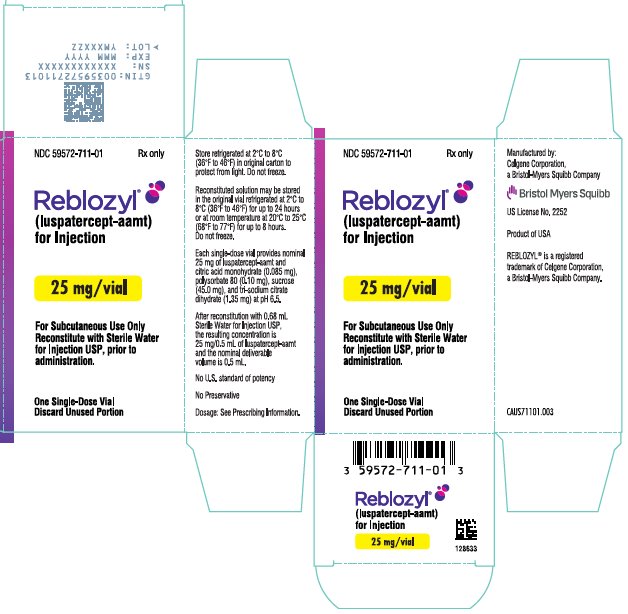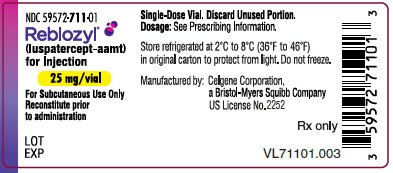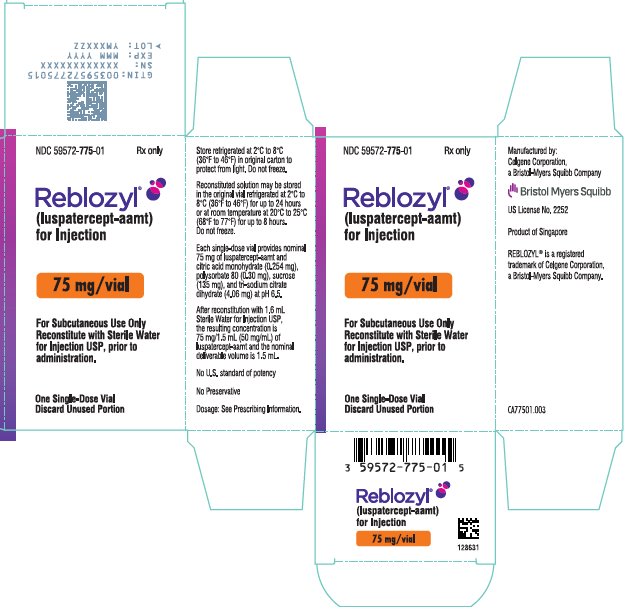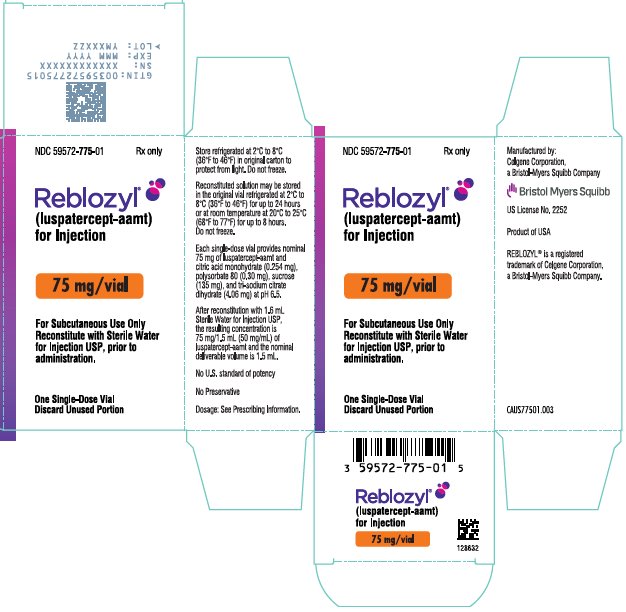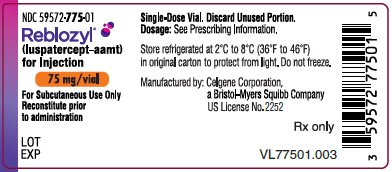 DRUG LABEL: Reblozyl
NDC: 59572-711 | Form: INJECTION, POWDER, LYOPHILIZED, FOR SOLUTION
Manufacturer: Celgene Corporation
Category: prescription | Type: HUMAN PRESCRIPTION DRUG LABEL
Date: 20240517

ACTIVE INGREDIENTS: LUSPATERCEPT 25 mg/1 1
INACTIVE INGREDIENTS: CITRIC ACID MONOHYDRATE; TRISODIUM CITRATE DIHYDRATE; POLYSORBATE 80; SUCROSE; HYDROCHLORIC ACID; SODIUM HYDROXIDE; WATER

HIGHLIGHTS OF PRESCRIBING INFORMATION

These highlights do not include all the information needed to use REBLOZYL safely and effectively. See full prescribing information for REBLOZYL.
REBLOZYL® (luspatercept-aamt) for injection, for subcutaneous use
Initial U.S. Approval: 2019

RECENT MAJOR CHANGES

Indications and Usage (1.2) | 8/2023
Dosage and Administration (2.2) | 8/2023
Warnings and Precautions, Hypertension (5.2) | 8/2023

1 INDICATIONS AND USAGE

REBLOZYL is an erythroid maturation agent indicated for the treatment of:

- Anemia in adult patients with beta thalassemia who require regular red blood cell (RBC) transfusions (1.1).
- Anemia without previous erythropoiesis stimulating agent use (ESA-naïve) in adult patients with very low- to intermediate-risk myelodysplastic syndromes (MDS) who may require regular red blood cell (RBC) transfusions (1.2).
- Anemia failing an erythropoiesis stimulating agent and requiring 2 or more RBC units over 8 weeks in adult patients with very low- to intermediate-risk myelodysplastic syndromes with ring sideroblasts (MDS-RS) or with myelodysplastic/myeloproliferative neoplasm with ring sideroblasts and thrombocytosis (MDS/MPN-RS-T) (1.3).
- Limitations of Use: REBLOZYL is not indicated for use as a substitute for RBC transfusions in patients who require immediate correction of anemia (1.4).

2 DOSAGE AND ADMINISTRATION

- The recommended starting dose is 1 mg/kg once every 3 weeks by subcutaneous injection (2.1, 2.2).
- Review hemoglobin (Hgb) results prior to each administration (2.1, 2.2).
- See full prescribing information for preparation and administration instructions (2.3).

3 DOSAGE FORMS AND STRENGTHS

- For injection: 25 mg lyophilized powder in a single-dose vial for reconstitution (3)
- For injection: 75 mg lyophilized powder in a single-dose vial for reconstitution (3)

4 CONTRAINDICATIONS

None (4).

5 WARNINGS AND PRECAUTIONS

- Thrombosis/Thromboembolism: Increased risk in patients with beta thalassemia. Monitor patients for signs and symptoms of thromboembolic events and institute treatment promptly (5.1).
- Hypertension: Monitor blood pressure (BP) during treatment. Initiate anti-hypertensive treatment if necessary (5.2).
- Extramedullary Hematopoietic (EMH) Masses: Increased risk in patients with beta thalassemia. Monitor patients for symptoms and signs or complications resulting from the EMH masses. Treat according to clinical guidelines and discontinue treatment in case of serious complications due to EMH masses (5.3).
- Embryo-Fetal Toxicity: May cause fetal harm. Advise females of reproductive potential of the potential risk to a fetus and use of effective contraception (5.4, 8.1, 8.3).

6 ADVERSE REACTIONS

The most common (>10%) adverse reactions were fatigue, headache, musculoskeletal pain, arthralgia, dizziness/vertigo, nausea, diarrhea, cough, abdominal pain, dyspnea, COVID-19, edema peripheral, hypertension, and hypersensitivity (6.1).

To report SUSPECTED ADVERSE REACTIONS, contact Bristol-Myers Squibb at 1-888-423-5436 or FDA at 1-800-FDA-1088 or www.fda.gov/medwatch.

8 USE IN SPECIFIC POPULATIONS

Lactation: Advise not to breastfeed (8.2).

FULL PRESCRIBING INFORMATION

1 INDICATIONS AND USAGE

1.1 Beta Thalassemia

REBLOZYL is indicated for the treatment of anemia in adult patients with beta thalassemia who require regular red blood cell (RBC) transfusions.

1.2 Myelodysplastic Syndromes Associated Anemia

REBLOZYL is indicated for the treatment of anemia without previous erythropoiesis stimulating agent use (ESA-naïve) in adult patients with very low- to intermediate-risk myelodysplastic syndromes (MDS) who may require regular red blood cell (RBC) transfusions.

1.3 Myelodysplastic Syndromes with Ring Sideroblasts or Myelodysplastic/ Myeloproliferative Neoplasm with Ring Sideroblasts and Thrombocytosis Associated Anemia

REBLOZYL is indicated for the treatment of anemia failing an erythropoiesis stimulating agent and requiring 2 or more red blood cell units over 8 weeks in adult patients with very low- to intermediate-risk myelodysplastic syndromes with ring sideroblasts (MDS-RS) or with myelodysplastic/myeloproliferative neoplasm with ring sideroblasts and thrombocytosis (MDS/MPN-RS-T).

1.4 Limitations of Use

REBLOZYL is not indicated for use as a substitute for RBC transfusions in patients who require immediate correction of anemia.

2 DOSAGE AND ADMINISTRATION

2.1 Recommended Dosage for Beta Thalassemia

The recommended starting dose of REBLOZYL is 1 mg/kg once every 3 weeks by subcutaneous injection for patients with beta thalassemia. Prior to each REBLOZYL dose, review the patient’s hemoglobin and transfusion record. Titrate the dose based on responses according to Table 1. Interrupt treatment for adverse reactions as described in Table 2. Discontinue REBLOZYL if a patient does not experience a decrease in transfusion burden after 9 weeks of treatment (administration of 3 doses) at the maximum dose level or if unacceptable toxicity occurs at any time.

If a planned administration of REBLOZYL is delayed or missed, administer REBLOZYL as soon as possible and continue dosing as prescribed, with at least 3 weeks between doses.

Dose Modifications for Response

Assess and review hemoglobin results prior to each administration of REBLOZYL. If an RBC transfusion occurred prior to dosing, use the pretransfusion hemoglobin for dose evaluation.

If a patient does not achieve a reduction in RBC transfusion burden after at least 2 consecutive doses (6 weeks) at the 1 mg/kg starting dose, increase the REBLOZYL dose to 1.25 mg/kg. Do not increase the dose beyond the maximum dose of 1.25 mg/kg. In the absence of transfusions, if hemoglobin increase is greater than 2 g/dL within 3 weeks or the predose hemoglobin is greater than or equal to 11.5 g/dL, reduce the dose or interrupt treatment with REBLOZYL as described in Table 1.

Dose level modifications for response are provided in Table 1.

Table 1: Beta Thalassemia - REBLOZYL Dose Titration for Response
 | REBLOZYL Dosing Recommendation*
Starting Dose | - 1 mg/kg every 3 weeks
Dose Increases for Insufficient Response at Initiation of Treatment
No reduction in RBC transfusion burden after at least 2 consecutive doses (6 weeks) at the 1 mg/kg starting dose | - Increase the dose to 1.25 mg/kg every 3 weeks
No reduction in RBC transfusion burden after 3 consecutive doses (9 weeks) at 1.25 mg/kg | - Discontinue treatment
Dose Modifications for Predose Hemoglobin Levels or Rapid Hemoglobin Rise
Predose hemoglobin is greater than or equal to 11.5 g/dL in the absence of transfusions | - Interrupt treatment - Restart when the hemoglobin is no more than 11 g/dL
Increase in hemoglobin greater than 2 g/dL within 3 weeks in the absence of transfusions and; - current dose is 1.25 mg/kg - current dose is 1 mg/kg - current dose is 0.8 mg/kg - current dose is 0.6 mg/kg | - Reduce dose to 1 mg/kg - Reduce dose to 0.8 mg/kg - Reduce dose to 0.6 mg/kg - Discontinue treatment
* Do not increase the dose if the patient is experiencing an adverse reaction as described in Table 2.

Dose Modifications for Toxicity

For patients experiencing Grade 3 or higher adverse reactions, modify treatment as described in Table 2.

Table 2: Beta Thalassemia - REBLOZYL Dosing Modifications for Adverse Reactions
 | REBLOZYL Dosing Recommendation*
Grade 3 or 4 hypersensitivity reactions | - Discontinue treatment
Other Grade 3 or 4 adverse reactions | - Interrupt treatment - Restart when the adverse reaction resolves to no more than Grade 1
Extramedullary hematopoietic (EMH) masses causing serious complications | - Discontinue treatment
* Grade 1 is mild, Grade 2 is moderate, Grade 3 is severe, and Grade 4 is life-threatening.

2.2 Recommended Dosage for Myelodysplastic Syndromes Associated Anemia

The recommended starting dosage of REBLOZYL is 1 mg/kg once every 3 weeks by subcutaneous injection for the treatment of anemia of MDS. Prior to each REBLOZYL dose, review the patient’s hemoglobin and transfusion record. Titrate the dose based on responses according to Table 3. Interrupt treatment for adverse reactions as described in Table 4. Discontinue REBLOZYL if a patient does not experience a decrease in transfusion burden including no increase from baseline hemoglobin after 9 weeks of treatment (administration of 3 doses) at the maximum dose level (1.75 mg/kg), or if unacceptable toxicity occurs at any time.

If a planned administration of REBLOZYL is delayed or missed, administer REBLOZYL as soon as possible and continue dosing as prescribed, with at least 3 weeks between doses.

Dose Modifications for Response

Assess and review hemoglobin results prior to each administration of REBLOZYL. If an RBC transfusion occurred prior to dosing, use the pretransfusion hemoglobin for dose evaluation.

If a patient is not RBC transfusion-free after at least 2 consecutive doses (6 weeks) at the 1 mg/kg starting dose, increase the REBLOZYL dose to 1.33 mg/kg (Table 3). If a patient is not RBC transfusion-free after at least 2 consecutive doses (6 weeks) at the 1.33 mg /kg dose level, increase the REBLOZYL dose to 1.75 mg/kg. Do not increase the dose more frequently than every 6 weeks (2 doses) or beyond the maximum dose of 1.75 mg/kg.

In the absence of transfusions, if hemoglobin increase is greater than 2 g/dL within 3 weeks or if the predose hemoglobin is greater than or equal to 11.5 g/dL, reduce the dose or interrupt treatment with REBLOZYL as described in Table 3. If, upon dose reduction, the patient loses response (i.e., requires a transfusion) or hemoglobin concentration drops by 1 g/dL or more in 3 weeks in the absence of transfusion, increase the dose by one dose level. Wait a minimum of 6 weeks between dose increases.

Dose modifications for response are provided in Table 3.

Table 3: MDS Associated Anemia - REBLOZYL Dose Titration for Response
 | REBLOZYL Dosing Recommendation*
Starting Dose | - 1 mg/kg every 3 weeks
Dose Increases for Insufficient Response at Initiation of Treatment
Not RBC transfusion-free after at least 2 consecutive doses (6 weeks) at the 1 mg/kg starting dose | - Increase the dose to 1.33 mg/kg every 3 weeks
Not RBC transfusion-free after at least 2 consecutive doses (6 weeks) at 1.33 mg/kg | - Increase the dose to 1.75 mg/kg every 3 weeks
No reduction in RBC transfusion burden including no increase from baseline hemoglobin after at least 3 consecutive doses (9 weeks) at 1.75 mg/kg | - Discontinue treatment
Dose Modifications for Predose Hemoglobin Levels or Rapid Hemoglobin Rise
Predose hemoglobin is greater than or equal to 11.5 g/dL in the absence of transfusions | - Interrupt treatment - Restart when the hemoglobin is no more than 11 g/dL
Increase in hemoglobin greater than 2 g/dL within 3 weeks in the absence of transfusions and; - current dose is 1.75 mg/kg - current dose is 1.33 mg/kg - current dose is 1 mg/kg - current dose is 0.8 mg/kg - current dose is 0.6 mg/kg | - Reduce dose to 1.33 mg/kg - Reduce dose to 1 mg/kg - Reduce dose to 0.8 mg/kg - Reduce dose to 0.6 mg/kg - Discontinue treatment
* Do not increase the dose if the patient is experiencing an adverse reaction as described in Table 4.

Dose Modifications for Toxicity

For patients experiencing Grade 3 or higher adverse reactions, modify treatment as described in Table 4.

Table 4: MDS Associated Anemia - REBLOZYL Dosing Modifications for Adverse Reactions
 | REBLOZYL Dosing Recommendation*
Grade 3 or 4 hypersensitivity reactions | - Discontinue treatment
Other Grade 3 or 4 adverse reactions | - Interrupt treatment - When the adverse reaction resolves to no more than Grade 1, restart treatment at the next lower dose level** - If the dose delay is > 12 consecutive weeks, discontinue treatment
* Grade 1 is mild, Grade 2 is moderate, Grade 3 is severe, and Grade 4 is life-threatening.
**Per Table 3 dose reductions above.

2.3 Preparation and Administration

REBLOZYL should be reconstituted and administered by a healthcare professional.

Reconstitute REBLOZYL with Sterile Water for Injection, USP only.

Table 5: Reconstitution Volumes
Vial Size | Amount of Sterile Water for Injection, USP required for reconstitution | Final Concentration | Deliverable Volume
25 mg vial | 0.68 mL | 25 mg/0.5 mL; (50 mg/mL) | 0.5 mL
75 mg vial | 1.6 mL | 75 mg/1.5 mL | 1.5 mL
 |  | (50 mg/mL)

Reconstitute the number of REBLOZYL vials to achieve the appropriate dose based on the patient’s weight. Use a syringe with suitable graduations for reconstitution to ensure accurate dosage.

Reconstitution Instructions

1. Reconstitute with Sterile Water for Injection, USP using volumes described in Table 5 (Reconstitution Volumes) with the stream directed onto the lyophilized powder. Allow to stand for one minute.
2. Discard the needle and syringe used for reconstitution. The needle and syringe used for reconstitution should not be used for subcutaneous injections.
3. Gently swirl the vial in a circular motion for 30 seconds. Stop swirling and let the vial sit in an upright position for 30 seconds.
4. Inspect the vial for undissolved particles in the solution. If undissolved powder is observed, repeat step 3 until the powder is completely dissolved.
5. Invert the vial and gently swirl in an inverted position for 30 seconds. Bring the vial back to the upright position, and let it sit for 30 seconds.
6. Repeat step 5 seven more times to ensure complete reconstitution of material on the sides of the vial.
7. Parenteral drug products should be inspected visually for particulate matter and discoloration prior to administration whenever solution and container permit. REBLOZYL is a colorless to slightly yellow, clear to slightly opalescent solution which is free of foreign particulate matter. Do not use if undissolved product or foreign particulate matter are observed.
8. If the reconstituted solution is not used immediately:
  1. Store at room temperature at 20°C to 25°C (68°F to 77°F) in the original vial for up to 8 hours. Discard if not used within 8 hours of reconstitution.
  2. Alternatively, store refrigerated at 2°C to 8°C (36°F to 46°F) for up to 24 hours in the original vial. Remove from refrigerated condition 15-30 minutes prior to injection to allow solution to reach room temperature for a more comfortable injection. Discard if not used within 24 hours of reconstitution.
  3. Do not freeze the reconstituted solution.

Discard any unused portion. Do not pool unused portions from the vials. Do not administer more than 1 dose from a vial. Do not mix with other medications.

Instructions for Subcutaneous Administration

Calculate the exact total dosing volume of 50 mg/mL solution required for the patient.

Slowly withdraw the dosing volume of the reconstituted REBLOZYL solution from the single-dose vial(s) into a syringe. Divide doses requiring larger reconstituted volumes (i.e., greater than 1.2 mL) into separate similar volume injections and inject into separate sites. If multiple injections are required, use a new syringe and needle for each subcutaneous injection.

Administer the injection subcutaneously into the upper arm, thigh, and/or abdomen.

3 DOSAGE FORMS AND STRENGTHS

- For injection: 25 mg white to off-white lyophilized powder in a single-dose vial for reconstitution.
- For injection: 75 mg white to off-white lyophilized powder in a single-dose vial for reconstitution.

4 CONTRAINDICATIONS

None.

5 WARNINGS AND PRECAUTIONS

5.1 Thrombosis/Thromboembolism

In adult patients with beta thalassemia, thromboembolic events (TEE) were reported in 8/223 (3.6%) REBLOZYL-treated patients. Reported TEEs included deep vein thromboses, pulmonary embolus, portal vein thrombosis, and ischemic strokes. Patients with known risk factors for thromboembolism, e.g. splenectomy or concomitant use of hormone replacement therapy, may be at further increased risk of thromboembolic conditions. Consider thromboprophylaxis in patients with beta thalassemia at increased risk of TEE.

Monitor patients receiving REBLOZYL for signs and symptoms of thromboembolic events and institute treatment promptly.

5.2 Hypertension

Hypertension was reported in 63/554 (11.4%) of REBLOZYL-treated patients. Across clinical studies, the incidence of Grade 3-4 hypertension ranged from 2% to 9.6%.

In adult patients with beta thalassemia with normal baseline blood pressure, 13 (6.2%) patients developed systolic blood pressure (SBP) ≥130 mm Hg and 33 (16.6%) patients developed diastolic blood pressure (DBP) ≥80 mm Hg.

In ESA-refractory or -intolerant adult patients with MDS with normal baseline blood pressure, 26 (30%) patients developed SBP ≥130 mm Hg and 23 (16%) patients developed DBP ≥80 mm Hg. In ESA-naïve adult patients with MDS with normal baseline blood pressure, 23 (36%) patients developed SBP ≥140 mm Hg and 11 (6%) patients developed DBP ≥80 mm Hg.

Monitor blood pressure prior to each administration. Manage new-onset hypertension or exacerbations of preexisting hypertension using anti-hypertensive agents.

5.3 Extramedullary Hematopoietic Masses

In adult patients with transfusion dependent beta thalassemia, EMH masses were observed in 3.2% of REBLOZYL-treated patients, with spinal cord compression symptoms due to EMH masses occurring in 1.9% of patients (BELIEVE and REBLOZYL long-term follow-up study).

In a study of adult patients with non-transfusion dependent beta thalassemia, a higher incidence of EMH masses was observed in 6.3% of REBLOZYL-treated patients vs. 2% of placebo-treated patients in the double-blind phase of the study, with spinal cord compression due to EMH masses occurring in 1 patient with a prior history of EMH. REBLOZYL is not indicated for use in patients with non-transfusion dependent beta-thalassemia.

Possible risk factors for the development of EMH masses in patients with beta thalassemia include history of EMH masses, splenectomy, splenomegaly, hepatomegaly, or low baseline hemoglobin (<8.5 g/dL). Signs and symptoms may vary depending on the anatomical location. Monitor patients with beta thalassemia at initiation and during treatment for symptoms and signs or complications resulting from the EMH masses and treat according to clinical guidelines. Discontinue treatment with REBLOZYL in case of serious complications due to EMH masses. Avoid use of REBLOZYL in patients requiring treatment to control the growth of EMH masses.

5.4 Embryo-Fetal Toxicity

Based on findings from animal reproductive studies, REBLOZYL may cause fetal harm when administered to a pregnant woman. In animal reproduction studies, administration of luspatercept-aamt to pregnant rats and rabbits during organogenesis resulted in adverse developmental outcomes including increased embryo-fetal mortality, alterations to growth, and structural abnormalities at exposures (based on area under the curve [AUC]) above those occurring at the maximum recommended human dose (MRHD) of 1.75 mg/kg.

Advise pregnant women of the potential risk to a fetus. Advise females of reproductive potential to use an effective method of contraception during treatment with REBLOZYL and for at least 3 months after the final dose [see Use in Specific Populations (8.1, 8.3)].

6 ADVERSE REACTIONS

The following clinically significant adverse reactions are described elsewhere in the labeling:

- Thrombosis/Thromboembolism [see Warnings and Precautions (5.1)]
- Hypertension [see Warnings and Precautions (5.2)]
- Extramedullary Hematopoietic Masses [see Warnings and Precautions (5.3)]

6.1 Clinical Trials Experience

Because clinical trials are conducted under widely varying conditions, adverse reaction rates observed in the clinical trials of a drug cannot be directly compared to rates in the clinical trials of another drug and may not reflect the rates observed in practice.

The data in the WARNINGS AND PRECAUTIONS reflect exposure to REBLOZYL as a single agent administered across a range of doses (0.125 mg/kg to 1.75 mg/kg) in 571 patients in 4 trials.

Beta Thalassemia

The safety of REBLOZYL in patients with beta thalassemia was evaluated in the BELIEVE trial [see Clinical Studies (14.1)].Key eligibility criteria included adult patients with beta thalassemia (with the exception of patients with hemoglobin S or alpha-thalassemia disease) without major organ damage or recent DVT stroke and platelet counts less than or equal to 1000 x 10^9/L.

Patients received a starting dose of REBLOZYL 1 mg/kg subcutaneous injection every 3 weeks. Overall, 53% of patients had their dose increased to 1.25 mg/kg (46% REBLOZYL, n = 223) or placebo (66%, n = 109). The median duration of treatment was similar between the REBLOZYL and placebo arms (63.3 weeks vs. 62.1 weeks, respectively). Per protocol, patients in the REBLOZYL and placebo arms were to remain on therapy for at least 48 weeks in the double-blind phase of the trial.

Among patients receiving REBLOZYL, 94% were exposed for 6 months or longer and 72% were exposed for greater than one year.

The median age of patients who received REBLOZYL was 30 years (range: 18, 66); 59% female; 54% White and 36% Asian.

Serious adverse reactions occurred in 3.6% of patients on REBLOZYL. Serious adverse reactions reported in 1% of patients were cerebrovascular accident and deep vein thrombosis. A fatal adverse reaction occurred in one patient treated with REBLOZYL who died due to an unconfirmed case of AML (M6).

Permanent discontinuation due to an adverse reaction (Grades 1-4) occurred in 5.4% of patients who received REBLOZYL. Most frequent adverse reactions requiring permanent discontinuation in patients who received REBLOZYL included arthralgia (1%), back pain (1%), bone pain (<1%), and headache (<1%).

Dosage reductions due to an adverse reaction occurred in 2.7% of patients who received REBLOZYL. Most frequent adverse reactions requiring dosage reduction in >0.5% of patients who received REBLOZYL included hypertension and headache.

Dosage interruptions due to an adverse reaction occurred in 15.2% of patients who received REBLOZYL. Most frequent adverse reactions requiring dosage interruption in >1% of patients who received REBLOZYL included upper respiratory tract infection, ALT increase, and cough.

The most common adverse reactions (at least 10% for REBLOZYL and 1% more than placebo) were headache (26%), bone pain (20%), arthralgia (19%), fatigue (14%), cough (14%), abdominal pain (14%), diarrhea (12%), and dizziness (11%).

Table 6 summarizes the adverse reactions in BELIEVE.

Table 6: Adverse Drug Reactions (>5%) in Patients with Beta Thalassemia Receiving REBLOZYL with a Difference Between Arms of 1% in BELIEVE Trial
Body System | REBLOZYL (N=223) |  | Placebo (N=109)
Adverse Reaction | All Grades n (%) | Grades ≥3a n (%) | All Grades n (%) | Grades ≥3 n (%)
Musculoskeletal and connective tissue disorders
Bone Pain | 44 (20) | 3 (1) | 9 (8) | 0 (0)
Arthralgia | 43 (19) | 0 (0) | 13 (12) | 0 (0)
Infections and infestation
Influenza | 19 (9) | 0 (0) | 6 (6) | 0 (0)
Viral Upper Respiratory Infection | 14 (6) | 1 (0.4) | 2 (2) | 0 (0)
Nervous system disorders
Headache | 58 (26) | 1 (<1) | 26 (24) | 1 (1)
Dizziness | 25 (11) | 0 (0) | 5 (5) | 0 (0)
General disorders and administration site conditions
Fatigue | 30 (14) | 0 (0) | 14 (13) | 0 (0)
Gastrointestinal disorders
Abdominal Pain b | 31 (14) | 0 (0) | 13 (12) | 0 (0)
Diarrhea | 27 (12) | 1 (<1) | 11 (10) | 0 (0)
Nausea | 20 (9) | 0 (0) | 6 (6) | 0 (0)
Vascular disorders
Hypertension c | 18 (8) | 4 (2) | 3 (3) | 0 (0)
Metabolism and nutrition disorders
Hyperuricemia | 16 (7) | 6 (3) | 0 (0) | 0 (0)
Respiratory, thoracic and mediastinal disorders
Cough | 32 (14) | 0 (0) | 12 (11) | 0 (0)
a Limited to Grade 3 reactions with the exception of 4 events of Grade 4 hyperuricemia.
b Grouped term includes abdominal pain and abdominal pain upper.
c Grouped term includes essential hypertension, hypertension, and hypertensive crisis.

Clinically relevant adverse reactions in <5% of patients include vertigo/vertigo positional, syncope/presyncope, injection site reactions, hypersensitivity, extramedullary hematopoietic masses, and spinal cord compression.

Liver function abnormalities in the BELIEVE trial are shown in Table 7.

Table 7: Liver Function Laboratory Abnormalities in Patients with Beta Thalassemia in the BELIEVE Trial
 | REBLOZYL N = 223 n (%) | Placebo N = 109 n (%)
ALT ≥ 3 × ULN | 26 (12) | 13 (12)
AST ≥ 3 × ULN | 25 (11) | 5 (5)
ALP ≥ 2 × ULN | 17 (8) | 1 (<1)
Total bilirubin ≥ 2 × ULN | 143 (64) | 51 (47)
Direct bilirubin ≥ 2 × ULN | 13 (6) | 4 (4)
ALP = alkaline phosphatase; ALT = alanine aminotransferase;
AST = aspartate aminotransferase; ULN = upper limit of normal.

Treatment of Myelodysplastic Syndromes Associated Anemia in ESA-naïve Patients

The safety of REBLOZYL in patients with very low‑ to intermediate‑risk myelodysplastic syndromes was evaluated in the COMMANDS trial in 356 randomized patients [see Clinical Studies (14.2)]. Key eligibility criteria included adult patients who were ESA‑naïve with endogenous sEPO levels of < 500 U/L and who required regular RBC transfusions.

The median time on treatment with REBLOZYL was 41.6 weeks (range, 0 – 165 weeks); 71.3% of patients were exposed for 24 weeks and 45.5% completed 48 weeks of treatment.

Among the 178 patients treated with REBLOZYL, 17 (9.6%) discontinued due to an adverse reaction, 48 (27%) had a dose interruption due to an adverse reaction, and 5 (2.8%) had a dose reduction due to an adverse reaction. The most common (>10%) all‑grade adverse reactions included diarrhea, fatigue, hypertension, edema peripheral, nausea, and dyspnea. The most common (>2%) Grade > 3 adverse reactions included hypertension and dyspnea. Selected laboratory abnormalities that changed from Grade 0‑2 at baseline to Grade > 2 at any time during the studies in at least 10% of patients were glomerular filtration rate and total bilirubin increased.

Table 8 shows the most common adverse reactions for patients treated with REBLOZYL or epoetin alfa in the COMMANDS trial [see Clinical Studies (14.2)].

Table 8: Adverse Reactions (≥5%) in Patients Receiving REBLOZYL in COMMANDS Trial
Body System /Adverse Reaction | REBLOZYL; (N=178) |  | Epoetin Alfa; (N=176)
Body System /Adverse Reaction | All Grades; n (%) | Grade ≥3; n (%) | All Grades; n (%) | Grade ≥3; n (%)
General disorders and administration site conditions
Fatigue a,b | 38 (22) | 0 (0) | 12 (7) | 0 (0)
Edema peripheral | 23 (13) | 0 (0) | 12 (7) | 0 (0)
Non-cardiac chest pain | 9 (5) | 1 (1) | 6 (3) | 0 (0)
Pyrexia | 9 (5) | 1 (1) | 12 (7) | 1 (1)
Gastrointestinal disorders
Diarrhea | 26 (15) | 0 (0) | 20 (11) | 0 (0)
Nausea | 21 (12) | 0 (0) | 13 (7) | 0 (0)
Vascular disorders
Hypertension a | 25 (14) | 17 (10) | 13 (7) | 9 (5)
Respiratory, thoracic and mediastinal disorders
Dyspnea | 21 (12) | 7 (4) | 13 (7) | 2 (1)
Dyspnea exertional | 9 (5) | 0 (0) | 1 (1) | 0 (0)
Nervous system disorders
Dizziness | 16 (9) | 1 (1) | 15 (9) | 0 (0)
Headache | 15 (8) | 0 (0) | 12 (7) | 1 (1)
Musculoskeletal and connective tissue disorders
Back Pain | 16 (9) | 2 (1) | 13 (7) | 3 (2)
Arthralgia | 10 (6) | 0 (0) | 14 (8) | 0 (0)
Myalgia | 9 (5) | 0 (0) | 5 (3) | 0 (0)
Osteoarthritis | 9 (5) | 1 (1) | 4 (2) | 0 (0)
Infections and infestations
COVID-19 | 19 (11) | 6 (3) | 17 (10) | 2 (1)
Urinary tract infection | 13 (7) | 0 (0) | 7 (4) | 0 (0)
Pneumonia | 8 (5) | 7 (4) | 15 (9) | 11 (6)
Metabolism and nutrition disorders
Hyperuricemia | 12 (7) | 1 (1) | 10 (6) | 1 (1)
Decreased appetite | 8 (5) | 0 (0) | 11 (6) | 0 (0)
Blood and lymphatic system disorders
Thrombocytopenia | 11 (6) | 7 (4) | 3 (2) | 1 (1)
Neutropenia | 9 (5) | 7 (4) | 13 (7) | 10 (6)
Psychiatric disorders
Insomnia | 9 (5) | 0 (0) | 6 (3) | 0 (0)
a Reaction includes similar/grouped terms.
b Includes asthenic conditions.

Other clinically relevant adverse reactions reported in <5% of patients are injection site reactions, including erythema, pruritus, and rash.

Shifts from Grades 0‑2 at baseline to Grades 2‑3 abnormalities for selected laboratory tests in the COMMANDS trial are shown in Table 9.

Table 9: Selected Treatment‑Emergent Laboratory Abnormalities in COMMANDS Trial that Shift to Grades 2‑3
Parameter | REBLOZYL |  | Epoetin Alfa
 | N a | n (%) | N a | n (%)
Total bilirubin | 171 | 38 (22) | 165 | 19 (12)
GFR b | 171 | 60 (35) | 167 | 36 (22)
a Number of patients at Grades 0-1 at baseline.
b GFR= glomerular filtration rate (mL/min)

Myelodysplastic Syndromes with Ring Sideroblasts or Myelodysplastic / Myeloproliferative Neoplasm with Ring Sideroblasts and Thrombocytosis Associated Anemia in ESA-refractory or -intolerant patients

The safety of REBLOZYL at the recommended dose and schedule was evaluated in 242 patients with MDS with ring sideroblasts (n=192) or other myeloid neoplasms (n=50) in the MEDALIST trial. The safety population included 63% males and 37% females of median age 72 years (range, 30 – 95 years); of these patients, 81% were White, 0.4% Black, 0.4% Other, and race was not reported in 18.2% of patients. The median time on treatment with REBLOZYL was 50.4 weeks (range, 3 – 221 weeks); 67% of patients were exposed for 6 months or longer and 49% were exposed for greater than one year.

Among the 242 patients treated with REBLOZYL, 5 (2.1%) had a fatal adverse reaction, 11 (4.5%) discontinued due to an adverse reaction, and 7 (2.9%) had a dose reduction due to an adverse reaction. The most common (≥10%) all-grade adverse reactions included fatigue, musculoskeletal pain, dizziness, diarrhea, nausea, hypersensitivity reactions, hypertension, headache, upper respiratory tract infection, bronchitis, and urinary tract infection. The most common (≥2%) Grade ≥ 3 adverse reactions included fatigue, hypertension, syncope and musculoskeletal pain. Selected laboratory abnormalities that changed from Grade 0-1 at baseline to Grade ≥ 2 at any time during the studies in at least 10% of patients included creatinine clearance decreased, total bilirubin increased, and alanine aminotransferase increased.

Table 10 shows the most common adverse reactions for patients treated with REBLOZYL or placebo through the first 8 cycles in the MEDALIST trial [see Clinical Studies (14.3)].

Table 10: Adverse Reactions (≥5%) in Patients Receiving REBLOZYL with a Difference Between Arms of >2% in MEDALIST Trial Through Cycle 8
Body System /Adverse Reaction | REBLOZYL (N=153) |  | Placebo (N=76)
Body System /Adverse Reaction | All Grades n (%) | Grade 3 n (%) | All Grades n (%) | Grade 3 n (%)
General disorders and administration site conditions
Fatigue a, b | 63 (41) | 11 (7) | 17 (22) | 2 (3)
Musculoskeletal and connective tissue disorders
Musculoskeletal pain b | 30 (20) | 3 (2) | 11 (14) | 0 (0)
Nervous system disorders
Dizziness/vertigo | 28 (18) | 1 (<1) | 5 (7) | 1 (1)
Headache b | 21 (14) | 0 (0) | 5 (7) | 0 (0)
Syncope / presyncope | 8 (5) | 5 (3) | 0 (0) | 0 (0)
Gastrointestinal disorders
Nausea b | 25 (16) | 1 (<1) | 8 (11) | 0 (0)
Diarrhea b | 25 (16) | 0 (0) | 7 (9) | 0 (0)
Respiratory, thoracic and mediastinal disorder
Dyspnea b | 20 (13) | 2 (1) | 4 (5) | 1 (1)
Immune system disorders
Hypersensitivity reactions b | 15 (10) | 1 (<1) | 5 (7) | 0 (0)
Renal and urinary disorders
Renal impairment b | 12 (8) | 3 (2) | 3 (4) | 0 (0)
Cardiac disorders
Tachycardia b | 12 (8) | 0 (0) | 1 (1) | 0 (0)
Injury poisoning and procedural complications
Injection site reactions | 10 (7) | 0 (0) | 3 (4) | 0 (0)
Infections and infestations
Upper respiratory tract infection | 10 (7) | 1 (<1) | 2 (3) | 0 (0)
Influenza / influenza like illness | 9 (6) | 0 (0) | 2 (3) | 0 (0)
a Includes asthenic conditions.
b Reaction includes similar/grouped terms.

Other clinically relevant adverse reactions reported in <5% of patients include bronchitis, urinary tract infection, and hypertension [see Warnings and Precautions (5.2)].

Shifts from Grades 0-1 to Grades 2-4 abnormalities for selected laboratory tests during the first 8 cycles in the MEDALIST trial are shown in Table 11.

Table 11: Selected Grades 2-4 Treatment-Emergent Laboratory Abnormalities Through Cycle 8 in the MEDALIST Trial
Parameter | REBLOZYL |  | Placebo
 | Na | n (%) | Na | n (%)
ALT elevated | 151 | 13 (9) | 74 | 5 (7)
AST elevated | 152 | 6 (4) | 76 | 0 (0)
Total bilirubin elevated | 140 | 17 (12) | 66 | 3 (5)
Creatinine clearance reduced | 113 | 30 (27) | 62 | 13 (21)
a Number of patients at Grades 0-1 at baseline.
ALT = alanine aminotransferase; AST = aspartate aminotransferase.

8 USE IN SPECIFIC POPULATIONS

8.1 Pregnancy

Risk Summary

Based on findings in animal reproduction studies, REBLOZYL may cause fetal harm when administered to a pregnant woman. There are no available data on REBLOZYL use in pregnant women to inform a drug-associated risk of major birth defects, miscarriage, or adverse maternal or fetal outcomes. In animal reproduction studies, administration of luspatercept-aamt to pregnant rats and rabbits during the period of organogenesis resulted in adverse developmental outcomes including embryo-fetal mortality, alterations to growth, and structural abnormalities at exposures (based on area under the curve [AUC]) above those occurring at the maximum recommended human dose (MRHD) (see Data). Advise pregnant women of the potential risk to a fetus.

The estimated background risk of major birth defects and miscarriage for the indicated population is unknown. All pregnancies have a background risk of birth defect, loss, or other adverse outcomes. In the U.S. general population, the estimated background risk of major birth defects and miscarriage in clinically recognized pregnancies is 2% to 4% and 15% to 20%, respectively.

Data

Animal Data

In embryo-fetal development studies, luspatercept-aamt was administered subcutaneously at 5, 15, or 30 mg/kg on gestation days 3 and 10 (rats) or 5, 20, or 40 mg/kg on gestation days 4 and 11 (rabbits). Effects in both species included reductions in numbers of live fetuses and fetal body weights, and increases in resorptions, post-implantation losses, and skeletal variations (such as asymmetric sternal centra in rats and angulated hyoid in rabbits). Effects were observed at exposures (based on AUC) approximately 7-times (rats) and 16-times (rabbits) the MRHD of 1.75 mg/kg.

In a pre- and postnatal development study, pregnant rats were administered luspatercept-aamt subcutaneously at 3, 10, or 30 mg/kg once every 2 weeks during organogenesis and through weaning, gestation day 6 through postnatal day 20. At all dose levels lower F1 pup body weights and adverse kidney findings (such as membranoproliferative glomerulonephritis, tubular atrophy/hypoplasia, and vessel ectasia occasionally associated with hemorrhage) were observed. These effects were observed at exposures (based on AUC) approximately 1.6-times the MRHD of 1.75 mg/kg.

8.2 Lactation

Risk Summary

Luspatercept-aamt was detected in milk of lactating rats. When a drug is present in animal milk, it is likely that the drug will be present in human milk. There are no data on the presence of REBLOZYL in human milk, the effects on the breastfed child, or the effects on milk production. Because of the potential for serious adverse reactions in the breastfed child, advise patients that breastfeeding is not recommended during treatment with REBLOZYL, and for 3 months after the last dose.

8.3 Females and Males of Reproductive Potential

Pregnancy Testing

Pregnancy testing is recommended for females of reproductive potential before starting REBLOZYL treatment.

Contraception

Females

REBLOZYL may cause embryo-fetal harm when administered to pregnant women [see Use in Specific Populations (8.1)]. Advise female patients of reproductive potential to use effective contraception during treatment with REBLOZYL and for at least 3 months after the last dose.

Infertility

Females

Based on findings in animals, REBLOZYL may impair female fertility [see Nonclinical Toxicology (13.1)]. Adverse effects on fertility in female rats were reversible after a 14-week recovery period.

8.4 Pediatric Use

Safety and effectiveness in pediatric patients have not been established. Based on findings in juvenile animals, REBLOZYL is not recommended for use in pediatric patients [see Non-Clinical Toxicology (13.1)].

8.5 Geriatric Use

Clinical studies of REBLOZYL in beta thalassemia did not include sufficient numbers of patients age 65 years and older to determine whether they respond differently from younger patients.

Clinical studies of REBLOZYL for treatment of anemia in ESA-naïve and ESA-refractory or -intolerant MDS included 347 (82%) patients ≥ 65 years of age and 167 (39%) patients ≥ 75 years of age. No differences in safety or effectiveness were observed between older (≥ 65 years) and younger patients.

9 DRUG ABUSE AND DEPENDENCE

9.1 Controlled Substance

REBLOZYL contains luspatercept-aamt, which is not a controlled substance.

9.2 Abuse

Abuse is the intentional, non-therapeutic use of a drug, even once, for its desirable psychological or physiological effects. Abuse of REBLOZYL may be seen in athletes for the effects on erythropoiesis to enhance athletic performance. Abuse of drugs that increase erythropoiesis, such as REBLOZYL, by healthy persons may lead to polycythemia, which may be associated with life-threatening cardiovascular complications (e.g., stroke, myocardial infarction, and thromboembolism).

Luspatercept-aamt and its metabolites neither selectively penetrate the central nervous system, nor produce behavioral effects in animals that are consistent with central nervous system activity.

11 DESCRIPTION

Luspatercept-aamt is an erythroid maturation agent. Luspatercept-aamt is a receptor fusion protein consisting of a modified extracellular domain of the human activin receptor type IIB linked to a human IgG1 Fc domain with a calculated molecular mass of approximately 76 kD. Luspatercept is produced in Chinese hamster ovary cells by recombinant DNA technology.

REBLOZYL (luspatercept-aamt) for injection is a sterile, preservative-free, white to off-white, lyophilized powder in single-dose vials for subcutaneous use after reconstitution.

Each 25 mg single-dose vial provides nominal 25 mg of luspatercept-aamt and citric acid monohydrate (0.085 mg), polysorbate 80 (0.10 mg), sucrose (45.0 mg), and tri-sodium citrate dihydrate (1.35 mg) at pH 6.5. After reconstitution with 0.68 mL Sterile Water for Injection USP, the resulting concentration is 25 mg/0.5 mL of luspatercept-aamt and the nominal deliverable volume is 0.5 mL.

Each 75 mg single-dose vial provides nominal 75 mg of luspatercept-aamt and citric acid monohydrate (0.254 mg), polysorbate 80 (0.30 mg), sucrose (135 mg), and tri-sodium citrate dihydrate (4.06 mg) at pH 6.5. After reconstitution with 1.6 mL Sterile Water for Injection USP, the resulting concentration is 75 mg/1.5 mL (50 mg/mL) of luspatercept-aamt and the nominal deliverable volume is 1.5 mL.

12 CLINICAL PHARMACOLOGY

12.1 Mechanism of Action

Luspatercept-aamt is a recombinant fusion protein that binds several endogenous TGF-β superfamily ligands, thereby diminishing Smad2/3 signaling. In models of β-thalassemia and MDS, luspatercept-aamt decreased abnormally elevated Smad2/3 signaling and improved hematology parameters associated with ineffective erythropoiesis in mice. Luspatercept-aamt promoted erythroid maturation through differentiation and increasing the percentage of late-stage erythroid precursors (normoblasts) in the bone marrow of mice and increased erythroid precursors in humans, thereby increasing erythropoiesis.

12.2 Pharmacodynamics

Increases in Hemoglobin in Patients with Low RBC Transfusion Burden

In patients having received < 4 units of RBC transfusion within 8 weeks prior to study, hemoglobin increased within 7 days of initiating REBLOZYL and correlated with the time to luspatercept-aamt maximum serum concentration (Cmax). The greatest hemoglobin (Hgb) increase occurred after the first dose; approximately 0.75 g/dL at a dose of 0.6 to 1.25 times the recommended starting dose for beta thalassemia, or approximately 1 g/dL at a dose of 0.75 to 1.75 times the recommended starting dose for MDS. Additional smaller increases were observed after subsequent doses. Hemoglobin levels returned to baseline approximately 6 to 8 weeks from the last dose following administration of luspatercept-aamt (0.6 to 1.75 mg/kg).

Increasing luspatercept-aamt serum exposure (AUC) was associated with greater Hgb increase in patients with beta thalassemia or MDS who had a baseline transfusion burden < 4 units/8 weeks. Increasing luspatercept-aamt serum exposure (time-averaged AUC) was associated with greater probability of achieving transfusion independence for at least 8 consecutive weeks in ESA-refractory or -intolerant patients with MDS requiring transfusions (≥ 2 units of RBC transfusion within 8 weeks).

12.3 Pharmacokinetics

Luspatercept-aamt exhibited linear pharmacokinetics (PK) over the dose range of 0.2 to 1.25 mg/kg (0.2 to 1.25 times the recommended starting dosage) in patients with beta thalassemia, and from 0.125 mg/kg to 1.75 mg/kg (0.125 to 1.75 times the recommended starting dosage) in patients with MDS. The geometric mean (% coefficient of variation [%CV]) steady-state AUC at the starting dose of 1 mg/kg was 126 (35.9%) day•µg/mL for patients with beta thalassemia and 154 (37.4%) day•µg/mL for patients with MDS. Luspatercept-aamt serum concentration reached steady state after 3 doses when administered every 3 weeks. The accumulation ratio of luspatercept-aamt was approximately 1.5.

Absorption

The median [range] time to maximum concentration (Tmax) of luspatercept-aamt was observed at approximately 5 [3 to 8] days post-dose in adult patients with beta thalassemia or 6 [3 to 7] days post-dose in adult patients with MDS. The absorption of luspatercept-aamt was not significantly affected by the subcutaneous injection sites (upper arm, thigh, or abdomen).

Distribution

The geometric mean (%CV) apparent volume of distribution (Vd/F) of luspatercept-aamt was 7.1 (26.7%) L for patients with beta thalassemia and 9.6 (26.7%) L for patients with MDS.

Elimination

The geometric mean (%CV) half-lives (t1/2) of luspatercept-aamt were approximately 11 (25.7%) days in patients with beta thalassemia and 14 (31.7%) days in patients with MDS. The geometric mean (%CV) apparent total clearance (CL/F) of luspatercept-aamt was 0.44 (38.5%) L/day in patients with beta thalassemia and 0.47 (42.9%) L/day in patients with MDS.

Metabolism

Luspatercept-aamt is expected to be catabolized into small peptides and amino acids by general catabolic degradation processes in multiple tissues.

Specific Populations

No clinically significant differences in the luspatercept-aamt PK were observed based on age (18 to 95 years), sex, race/ethnicity (Asian, White), mild to severe hepatic impairment (total bilirubin ≤ upper limit of normal [ULN] and aspartate aminotransaminase [AST] or alanine transaminase [ALT] > ULN, or total bilirubin > ULN and any AST or ALT), mild to moderate renal impairment (estimated glomerular filtration rate [eGFR] 30 to 89 mL/min), baseline albumin (30 to 56 g/L), baseline serum erythropoietin (2.4 to 2920 U/L), red blood cell (RBC) transfusion burden (0 to 43 units/24 weeks), beta thalassemia genotype (β0/β0 vs. non-β0/β0), splenectomy, and ring sideroblasts status in MDS (negative vs. positive). The effect of AST or ALT >3 x ULN and the effect of severe renal impairment (eGFR <30 mL/min) on luspatercept-aamt PK is unknown.

Body Weight

The apparent CL/F and Vd/F of luspatercept-aamt increased with increasing body weight in patients with beta thalassemia (34 to 97 kg) and in patients with MDS (33 to 124 kg).

Drug Interaction Studies

Effect of Iron-chelating Agents on Luspatercept-aamt

No clinically significant differences in luspatercept-aamt PK were observed when used concomitantly with iron-chelating agents.

12.6 Immunogenicity

The observed incidence of anti-drug antibodies (ADA) is highly dependent on the sensitivity and specificity of the assay. Differences in assay methods preclude meaningful comparisons of the incidence of anti-drug antibodies in the studies described below with the incidence of anti-drug antibodies in other studies, including those of REBLOZYL or of other luspatercept products.

In the BELIEVE trial, the median duration of exposure was 64 weeks, with a median ADA sampling period of 50 weeks. Of the 220 patients in the BELIEVE trial with beta thalassemia who require regular RBC transfusions treated with REBLOZYL and evaluable for the presence of anti-luspatercept-aamt antibodies, 4 patients (1.81%) tested positive for treatment-emergent anti-luspatercept-aamt antibodies, including 2 patients (0.9%) who had neutralizing antibodies detected. The majority of anti-luspatercept-aamt antibodies were of low titers.

In the COMMANDS trial, the median duration of exposure was 42 weeks, with the median ADA sampling period of 27 weeks. In the MEDALIST trial, the median duration of exposure was 49 weeks, with the median ADA sampling period of 46 weeks. Of the 331 ESA-naïve (COMMANDS trial) and ESA-refractory or -intolerant (MEDALIST trial) patients with MDS who were treated with REBLOZYL, 21 patients (6.3%) tested positive for treatment-emergent anti-luspatercept-aamt antibodies, including 14 patients (4.2%) who had neutralizing antibodies. The majority of anti-luspatercept-aamt antibodies were of low titers.

There were no severe acute systemic hypersensitivity reactions reported for patients with anti-luspatercept-aamt antibodies in REBLOZYL clinical trials, and there was no association between hypersensitivity type reaction or injection site reaction and presence of anti-luspatercept-aamt antibodies. There was no apparent effect of anti-luspatercept-aamt antibodies on clinical response.

Anti-Drug Antibody Effects on Pharmacokinetics

Among patients in the BELIEVE trial with luspatercept-aamt exposure data available, luspatercept‑aamt mean trough concentration (Ctrough) was approximately 35% lower in 4 patients with beta thalassemia who tested positive for treatment‑emergent anti‑luspatercept‑aamt antibodies (2.19 μg/mL) compared to patients with beta thalassemia who did not develop treatment‑emergent anti‑luspatercept‑aamt antibodies (3.38 μg/mL). There is insufficient data to assess whether the observed anti-luspatercept-aamt antibody associated pharmacokinetic changes reduce effectiveness in patients with beta thalassemia.

Among 21 ESA-naïve and ESA-refractory or -intolerant patients with MDS in the COMMANDS and MEDALIST trials who tested positive for treatment-emergent anti‑luspatercept‑aamt antibodies, there were no identified clinically significant effects of anti‑luspatercept‑aamt antibodies on pharmacokinetics, pharmacodynamics, safety, or effectiveness of luspatercept‑aamt over the treatment duration.

13 NONCLINICAL TOXICOLOGY

13.1 Carcinogenesis, Mutagenesis, Impairment of Fertility

No carcinogenicity or mutagenicity studies have been conducted with luspatercept-aamt.

In a repeat-dose toxicity study, juvenile rats were administered luspatercept-aamt subcutaneously at 1, 3, or 10 mg/kg once every 2 weeks from postnatal day 7 to 91. Hematologic malignancies (granulocytic leukemia, lymphocytic leukemia, malignant lymphoma) were observed at 10 mg/kg resulting in exposures (based on area under the curve [AUC]) approximately 4.4 times the maximum recommended human dose (MRHD) of 1.75 mg/kg.

In a combined male and female fertility and early embryonic development study in rats, luspatercept-aamt was administered subcutaneously to animals at doses of 1 to 15 mg/kg. There were significant reductions in the average numbers of corpora lutea, implantations, and viable embryos in luspatercept-aamt-treated females. Effects on female fertility were observed at the highest dose with exposures (based on AUC) approximately 7-times the MRHD of 1.75 mg/kg. Adverse effects on fertility in female rats were reversible after a 14-week recovery period. No adverse effects were noted in male rats.

14 CLINICAL STUDIES

14.1 Beta Thalassemia

The efficacy of REBLOZYL was evaluated in adult patients with beta thalassemia in the BELIEVE trial (NCT02604433). BELIEVE was a multicenter, randomized, double-blind, placebo-controlled trial in which (n=336) patients with beta thalassemia requiring regular red blood cell transfusions (6-20 RBC units per 24 weeks) with no transfusion-free period greater than 35 days during that period were randomized 2:1 to REBLOZYL (n=224) or placebo (n=112). In BELIEVE, REBLOZYL was administered subcutaneously once every 3 weeks as long as a reduction in transfusion requirement was observed or until unacceptable toxicity. All patients were eligible to receive best supportive care, which included RBC transfusions; iron-chelating agents; use of antibiotic, antiviral, and antifungal therapy; and/or nutritional support, as needed.

The BELIEVE trial excluded patients with a diagnosis of Hemoglobin S/β-thalassemia or isolated alpha (α)-thalassemia (e.g., Hemoglobin H) or who had major organ damage (liver disease, heart disease, lung disease, renal insufficiency). Patients with recent deep vein thrombosis or stroke or recent use of ESA, immunosuppressant, or hydroxyurea therapy were also excluded. The median age was 30 years (range: 18-66). The trial was comprised of patients who were 42% male, 54.2% White, 34.8% Asian, and 0.3% Black or African American. The percent of patients reporting their race as “other” was 7.7%, and race was not collected or reported for 3% of patients.

Table 12 summarizes the baseline disease-related characteristics in the BELIEVE study.

Table 12: Baseline Disease Characteristics of Patients with Beta Thalassemia in BELIEVE
Disease Characteristic | REBLOZYL (N=224) | Placebo (N=112)
Beta thalassemia diagnosis, n (%)
Beta-thalassemia | 174 (77.7) | 83 (74.1)
HbE/beta thalassemia | 31 (13.8) | 21 (18.8)
Beta thalassemia combined with alpha-thalassemia | 18 (8) | 8 (7.1)
Missing a | 1 (0.4) | 0
Baseline transfusion burden 12 weeks prior to randomization
Median (min, max) (Units/12 weeks) | 6.12 (3, 14) | 6.27 (3, 12)
Beta thalassemia gene mutation grouping, n (%)
β0/β0 | 68 (30.4) | 35 (31.3)
Non-β0/β0 | 155 (69.2) | 77 (68.8)
Missing a | 1 (0.4) | 0
Baseline serum ferritin level (μg/L)
N | 220 | 111
Median (min, max) | 1441.25 (88, 6400) | 1301.50 (136, 6400)
Splenectomy, n (%)
Yes | 129 (57.6) | 65 (58)
No | 95 (42.4) | 47 (42)
Age patient started regular transfusions (years)
N | 169 | 85
Median (min, max) | 2 (0, 52) | 2 (0, 51)
HbE=hemoglobin E.
a "Missing" category includes patients in the population who had no result for the parameter listed.

The efficacy of REBLOZYL in adult patients with beta thalassemia was established based upon the proportion of patients achieving RBC transfusion burden reduction (≥33% reduction from baseline) with a reduction of at least 2 units from Week 13 to Week 24.

Efficacy results are shown in Table 13.

Table 13: Efficacy Results in Beta Thalassemia - BELIEVE
Endpoint | REBLOZYL (N=224) | Placebo (N=112) | Risk Difference (95% CI) | p-value
≥33% Reduction from baseline in RBC transfusion burden with a reduction of at least 2 units for 12 consecutive weeks
Primary endpoint – Week 13 to Week 24 | 47 (21.0) | 5 (4.5) | 16.5 (9.9, 23.1) | <0.0001
Week 37 to Week 48 | 44 (19.6) | 4 (3.6) | 16.1 (9.8, 22.4) | <0.0001
≥50% Reduction from baseline in RBC transfusion burden with a reduction of at least 2 units for 12 consecutive weeks
Week 13 to Week 24 | 16 (7.1) | 2 (1.8) | 5.4 (1.2, 9.5) | 0.0402
Week 37 to Week 48 | 23 (10.3) | 1 (0.9) | 9.4 (5, 13.7) | 0.0017

14.2 Treatment of Myelodysplastic Syndromes with Associated Anemia in ESA-naïve Patients

The efficacy of REBLOZYL was evaluated in the COMMANDS trial (NCT03682536), a multi‑center, open‑label, randomized active‑controlled trial comparing REBLOZYL versus epoetin alfa in patients with anemia due to IPSS‑R very low, low, or intermediate‑risk myelodysplastic syndromes or with myelodysplastic/myeloproliferative neoplasm with ring sideroblasts and thrombocytosis (MDS/MPN RS‑T) in ESA‑naïve patients (with endogenous sEPO levels of < 500 U/L) who require regular red blood cell transfusions. For eligibility, patients were required to have had 2 to 6 RBC units/8 weeks confirmed for a minimum of 8 weeks immediately preceding randomization.

The COMMANDS trial included 356 patients randomized 1:1 to REBLOZYL (N=178) or epoetin alfa (N=178). Randomization was stratified by RBC transfusion burden, RS status, and endogenous serum erythropoietin (sEPO) level at baseline. Treatment was started at 1 mg/kg subcutaneously every 3 weeks. Two dose level increases were allowed (to 1.33 mg/kg and to 1.75 mg/kg). Doses were held and subsequently reduced for adverse reactions, reduced if the hemoglobin increased by ≥ 2 g/dL from the prior cycle, and held if the predose hemoglobin was ≥ 12 g/dL.

All patients received best supportive care, which included RBC transfusions as needed. Patients were treated for 24 weeks and were assessed for efficacy at that time point. Treatment beyond 24 weeks was optional based upon response to treatment and absence of disease progression.

The median age of the 356 study participants was 74 years (range: 33, 93 years). The trial population was 56% male and 44% female; 79.5% were White, 0.6% Black or African American, 12.1% Asian, and race was not reported in 7.9% of patients. Ethnicities were reported as 85.4% for Not Hispanic or Latino patients, 6.5% for Hispanic or Latino patients, 7.6% for patients with no ethnicity reported, and 0.6% were unknown. IPSS‑R risk classification at baseline was 9.3% very low, 72.2% low, 17.4% intermediate, 0.3% high, and 0.8% missing. Table 14 summarizes the baseline disease‑related characteristics in the COMMANDS study.

Table 14: Baseline Disease Characteristics of Patients in COMMANDS
Disease Characteristic | REBLOZYL; (N=178) | Epoetin Alfa; (N=178)
Hemoglobin (g/dL) – n (%)
Median (min, max) | 7.80 (4.7, 9.2) | 7.80 (4.5, 10.2)
Serum EPO (U/L) – n (%)
Median (min, max) | 78.7 (7.8, 495.8) | 85.9 (4.6, 462.5)
IPSS-R risk classification at baseline – n (%)
Very low | 16 (9.0) | 17 (9.6)
Low | 126 (70.8) | 131 (73.6)
Intermediate | 34 (19.1) | 28 (15.7)
High | 1 (0.6) | 0 (0)
Missing | 1 (0.6) | 2 (1.1)
Ring sideroblast status (per WHO criteria) – n (%)
RS+ | 130 (73.0) | 128 (71.9)
RS- | 48 (27.0) | 49 (27.5)
Missing | 0 (0) | 1 (0.6)
SF3B1 mutation status – n (%)
Mutated | 111 (62.4) | 99 (55.6)
Non-mutated | 65 (36.5) | 72 (40.4)
Missing | 2 (1.1) | 7 (3.9)

The efficacy of REBLOZYL in the treatment of anemia in ESA‑naïve adult patients with MDS was established at the time of the interim efficacy analysis based upon the proportion of patients who experienced both red blood cell transfusion independence (RBC‑TI) [defined as the absence of any RBC transfusion during any consecutive 12‑week period] and an associated concurrent mean improvement in hemoglobin by at least 1.5 g/dL for any consecutive 12 week period during Weeks 1-24.

At the time of the interim efficacy analysis, 301 subjects were included in the efficacy analysis, of which 147 were in the luspatercept arm and 154 were in the epoetin alfa arm, which is about 85% of the total information. The key efficacy results are shown in Table 15.

Table 15: Key Efficacy Results in COMMANDS
Endpoint | REBLOZYL; (N=147) | Epoetin Alfa a; (N=154)
RBC-TI for ≥12 weeks with associated concurrent mean Hgb increase of ≥ 1.5 g/dL (Weeks 1-24)
Response rate, n (%); (95% CI) | 86 (58.5); (50.1, 66.6) | 48 (31.2); (24.0, 39.1)
Common Rate Difference (95% CI) b | 26.6 (15.8, 37.4)
p-value c | <0.0001
Mean Hgb increase ≥ 1.5 g/dL (Weeks 1-24)
Response rate, n (%); (95% CI) | 106 (72.1); (64.1, 79.2) | 75 (48.7); (40.6, 56.9)
Common Rate Difference (95% CI) b | 23.2 (12.2, 34.1)
HI-E per IWG ≥8 weeks (Weeks 1-24)
Response rate, n (%); (95% CI) | 109 (74.1); (66.3, 81.0) | 79 (51.3); (43.1, 59.4)
Common Rate Difference (95% CI) b | 22.3 (11.8, 32.8)
p-value c | <0.0001
RBC-TI for 24 weeks (Weeks 1-24)
Response rate, n (%); (95% CI) | 70 (47.6); (39.3, 56.0) | 45 (29.2); (22.2, 37.1)
Common Rate Difference (95% CI) b | 17.0 (6.7, 27.2)
p-value c | 0.0012
RBC-TI for ≥12 weeks (Weeks 1-24)
Response rate, n (%); (95% CI) | 98 (66.7); (58.4, 74.2) | 71 (46.1); (38.1, 54.3)
Common Rate Difference (95% CI) b | 19.1 (8.6, 29.6)
p-value c | 0.0003
EOT = End of treatment; HI-E = Hematologic Improvement – Erythroid Response; NE = Not Estimable; RBC-TI = red blood cell transfusion independence
a The majority of study participants (>90%) were outside of the United States and a non-U.S.-licensed epoetin alfa product was used in the control arm for such patients. Direct comparisons have not been established between REBLOZYL and U.S. licensed epoetin alfa product for the treatment of patients with anemia due to IPSS-R very low, low, or intermediate-risk myelodysplastic syndromes or MDS/MPN RS-T in ESA-naïve patients.
b Common rate difference is based on the Mantel-Haenszel stratum weights.
c Based on CMH test stratified by baseline RBC transfusion burden (< 4, ≥ 4 pRBC units), RS status (RS+, RS-) and sEPO level (≤ 200, > 200 U/L). 2-sided p-value is presented. The statistical significance level at the second interim analysis is two-sided p-value 0.03.

No major outliers were observed in clinically relevant baseline demographic and disease characteristic subgroups.

14.3 Myelodysplastic Syndromes with Ring Sideroblasts or Myelodysplastic/Myeloproliferative Neoplasm with Ring Sideroblasts and Thrombocytosis Associated Anemia in ESA-refractory or -intolerant Patients

The efficacy of REBLOZYL was evaluated in the MEDALIST trial (NCT02631070), a multi-center, randomized, double-blind, placebo-controlled trial in patients with IPSS-R very low, low, or intermediate-risk myelodysplastic syndromes who have ring sideroblasts and require red blood cell transfusions (2 or more RBC units over 8 weeks). For eligibility, patients were required to have had an inadequate response to prior treatment with an erythropoiesis-stimulating agent (ESA), be intolerant of ESAs, or have a serum erythropoietin > 200 U/L. The MEDALIST trial excluded patients with deletion 5q (del 5q), white blood cell count > 13 Gi/L, neutrophils < 0.5 Gi/L, platelets < 50 Gi/L, or with prior use of a disease modifying agent for treatment of MDS.

The MEDALIST trial included 229 patients randomized 2:1 to REBLOZYL (n=153) or placebo (n=76). Randomization was stratified by baseline RBC transfusion burden and baseline IPSS-R. Treatment was started at 1 mg/kg subcutaneously every 3 weeks; the dose could be increased after completion of the first 2 cycles if the patient had at least one RBC transfusion in the prior 6 weeks. Two dose level increases were allowed (to 1.33 mg/kg and to 1.75 mg/kg). Doses were held and subsequently reduced for adverse reactions, reduced if the hemoglobin increased by ≥ 2 g/dL from the prior cycle, and held if the predose hemoglobin was ≥ 11.5 g/dL.

All patients received best supportive care, which included RBC transfusions as needed. The primary efficacy assessment was conducted after completion of 24 weeks on study drug. Patients with a decrease in transfusion requirement or increase in hemoglobin could continue on blinded study drug thereafter until unacceptable toxicity, loss of efficacy, or disease progression.

The median age of the 229 study participants was 71 years (range: 26, 95 years). The trial population was 63% male and 69% White. Table 16 summarizes the baseline disease-related characteristics in the MEDALIST study.

Table 16: Baseline Disease Characteristics of Patients in MEDALIST
Disease Characteristic | REBLOZYL (N=153) | Placebo (N=76)
Time Since Original MDS Diagnosis a (months)
Median (range) | 44.0 (3, 421) | 36.1 (4, 193)
Serum EPO (U/L) Categories b, n (%)
< 200 | 88 (57.5) | 50 (65.8)
200 to 500 | 43 (28.1) | 15 (19.7)
> 500 | 21 (13.7) | 11 (14.5)
Missing | 1 (0.7) | 0
Diagnosis per WHO Criteria, n (%)
MDS-RS c | 135 (88.2) | 65 (85.5)
MDS/MPN-RS-T | 14 (9.2) | 9 (11.8)
Other d | 4 (2.6) | 2 (2.6)
IPSS-R Classification Risk Category, n (%)
Very low | 18 (11.8) | 6 (7.9)
Low | 109 (71.2) | 57 (75)
Intermediate | 25 (16.3) | 13 (17.1)
High | 1 (0.7) | 0
RBC Transfusions/8 Weeks Over 16 Weeks Categories, n (%)
< 4 units | 46 (30.1) | 20 (26.3)
≥ 4 and < 6 units | 41 (26.8) | 23 (30.3)
≥ 6 units | 66 (43.1) | 33 (43.4)
EPO=erythropoietin; IPSS R=International Prognostic Scoring System-Revised; ITT=intent-to-treat; MDS=myelodysplastic syndromes; RARS=refractory anemia with ring sideroblasts; RBC=red blood cell; RCMD=refractory cytopenia with multilineage dysplasia; SD=standard deviation; WHO=World Health Organization.
a Time since original MDS diagnosis was defined as the number of years from the date of original diagnosis to the date of informed consent.
b Baseline EPO was defined as the highest EPO value within 35 days of the first dose of study drug.
c Includes MDS-RS-MLD and MDS-RS-SLD.
d Includes MDS-EB-1, MDS-EB-2, and MDS-U.

The efficacy of REBLOZYL in adult patients with MDS-RS and MDS-RS-T was established based upon the proportion of patients who were red blood cell transfusion independent (RBC-TI), defined as the absence of any RBC transfusion during any consecutive 8-week period occurring entirely within Weeks 1 through 24.

The efficacy results are shown in Tables 17 and 18.

Table 17: Efficacy Results in MEDALIST
Endpoint | REBLOZYL (N=153) n, % (95% CI) | Placebo (N=76) n, % (95% CI) | Common Risk Difference (95% CI) | p-value
RBC-TI ≥ 8 weeks during Weeks 1-24 | 58 (37.9) (30.2, 46.1) | 10 (13.2) (6.5, 22.9) | 24.6 (14.5, 34.6) | <0.0001
RBC-TI ≥ 12 weeks during Weeks 1-24 | 43 (28.1) (21.1, 35.9) | 6 (7.9) (3.0, 16.4) | 20.0 (10.9, 29.1) | 0.0002
RBC-TI ≥ 12 weeks during Weeks 1-48* | 51 (33.3) (25.9, 41.4) | 9 (11.8) (5.6, 21.3) | 21.4 (11.2, 31.5) | 0.0003
* The median (range) duration of treatment was 49 weeks (6 to 114 weeks) on the REBLOZYL arm and 24 weeks (7 to 89 weeks) on the placebo arm.

Table 18 shows the proportion of patients who achieved RBC-TI ≥ 8 weeks during Weeks 1-24 by diagnosis and baseline transfusion requirement.

Table 18: RBC-TI ≥ 8 Weeks during Weeks 1-24 By Diagnosis and Baseline Transfusion Burden in MEDALIST
 | Responders / N |  | % Response (95% CI)
 | REBLOZYL | Placebo | REBLOZYL | Placebo
WHO 2016 Diagnosis
MDS-RS | 46 / 135 | 8 / 65 | 34.1 (26.1, 42.7) | 12.3 (5.5, 22.8)
MDS/MPN-RS-T | 9 / 14 | 2 / 9 | 64.3 (35.1, 87.2) | 22.2 (2.8, 60.0)
Other a | 3 / 4 | 0 / 2 | 75.0 (19.4, 99.4) | 0.0 (0.0, 84.2)
Baseline RBC Transfusion Burden
2 - 3 units/8 weeks b | 37 / 46 | 8 / 20 | 80.4 (66.1, 90.6) | 40.0 (19.1, 63.9)
4 - 5 units/8 weeks c | 15 / 41 | 1 / 23 | 36.6 (22.1, 53.1) | 4.3 (0.1, 21.9)
≥ 6 units/8 weeks | 6 / 66 | 1 / 33 | 9.1 (3.4, 18.7) | 3.0 (0.1, 15.8)
a Includes MDS-EB-1, MDS-EB-2, and MDS-U.
b Includes patients who received 3.5 units.
c Includes patients who received 5.5 units.

16 HOW SUPPLIED/STORAGE AND HANDLING

16.1 How Supplied

REBLOZYL (luspatercept-aamt) for injection is a white to off-white lyophilized powder supplied in a single-dose vial. Each carton contains one vial.

REBLOZYL 25 mg/vial (NDC 59572-711-01)
REBLOZYL 75 mg/vial (NDC 59572-775-01)

16.2 Storage

Store vials refrigerated at 2°C to 8°C (36°F to 46°F) in original carton to protect from light. Do not freeze.

17 PATIENT COUNSELING INFORMATION

Discuss the following with patients prior to and during treatment with REBLOZYL.

Thromboembolic Events

Advise beta thalassemia patients of the potential risk of thromboembolic events. Review known risk factors for developing thromboembolic events and advise patients to reduce modifiable risk factors (e.g., smoking, use of oral contraceptives) [see Warnings and Precautions (5.1)].

Effects on Blood Pressure

Caution patients that REBLOZYL may cause an increase in blood pressure [see Warnings and Precautions (5.2)].

Extramedullary Hematopoietic Masses

Advise patients with beta thalassemia of the potential risk of extramedullary hematopoietic masses. Review possible risk factors for developing extramedullary hematopoietic masses. Instruct patients to report possible signs and symptoms of EMH masses [see Warnings and Precautions (5.3)].

Embryo-Fetal Toxicity

Advise females of reproductive potential of the potential risk to a fetus. Advise females of reproductive potential to use effective contraception while receiving REBLOZYL and for at least 3 months after the final dose. Advise females to contact their healthcare provider if they become pregnant, or if pregnancy is suspected, during treatment with REBLOZYL [see Warnings and Precautions (5.4) and Use in Specific Populations (8.1)].

Lactation

Advise females not to breastfeed during treatment with REBLOZYL and for 3 months after the final dose [see Use in Specific Populations (8.2)].

Manufactured by:
Celgene Corporation, a Bristol-Myers Squibb Company
86 Morris Avenue
Summit, NJ 07901
U.S. License No. 2252

REBLOZYL® is a registered trademark of Celgene Corporation, a Bristol-Myers Squibb Company.

REBPI.007

PATIENT INFORMATION
REBLOZYL® (REB-low-zil)
(luspatercept-aamt)
for injection, for subcutaneous use

What is REBLOZYL?

REBLOZYL is a prescription medicine used to treat anemia (low red blood cells) in adults with:

- beta thalassemia who need regular red blood cell (RBC) transfusions.
- myelodysplastic syndromes who may need regular RBC transfusions and have never received an erythropoiesis stimulating agent (ESA).
- myelodysplastic syndromes with ring sideroblasts (MDS-RS) or myelodysplastic/myeloproliferative neoplasms with ring sideroblasts and thrombocytosis (MDS/MPN-RS-T) who need 2 or more RBC units over 8 weeks and have not responded well to an ESA.

REBLOZYL is not for use as a substitute for RBC transfusions in people who need immediate treatment for anemia.
It is not known if REBLOZYL is safe and effective in children.

Before receiving REBLOZYL, tell your healthcare provider about all of your medical conditions, including if you:

- have or have had blood clots
- take hormone replacement therapy or birth control pills (oral contraceptives)
- have had your spleen removed (splenectomy)
- smoke
- have or have had high blood pressure (hypertension)
- have a history of extramedullary hematopoietic (EMH) masses
- have or have had enlarged spleen or liver
- are pregnant or plan to become pregnant. REBLOZYL may harm your unborn baby. Tell your healthcare provider right away if you become pregnant or think you may be pregnant during treatment with REBLOZYL.
  Females who are able to become pregnant:
  - Your healthcare provider should do a pregnancy test before you start treatment with REBLOZYL.
  - You should use effective birth control (contraception) during treatment with REBLOZYL and for at least 3 months after the last dose.
- are breastfeeding or plan to breastfeed. It is not known if REBLOZYL passes into your breast milk.
  - Do not breastfeed during treatment with REBLOZYL and for 3 months after the last dose. Talk to your healthcare provider about the best way to feed your baby during this time.

Tell your healthcare provider about all the medicines you take, including prescription and over-the-counter medicines, vitamins, and herbal supplements.

How will I receive REBLOZYL?

- Your healthcare provider will prescribe REBLOZYL in a dose that is right for you. Depending on how you respond to REBLOZYL, your healthcare provider may adjust your dose or stop treatment.
- REBLOZYL is given as an injection under your skin (subcutaneous) in the upper arm, thigh, or stomach (abdomen) by your healthcare provider.
- Your healthcare provider will do regular blood tests to check your hemoglobin to monitor if your anemia is getting better before each injection and during your treatment with REBLOZYL.

If your scheduled REBLOZYL dose is delayed or missed, your healthcare provider will give your dose of REBLOZYL as soon as possible and continue your treatment as prescribed with at least 3 weeks between doses.

What are the possible side effects of REBLOZYL?
REBLOZYL may cause serious side effects, including:

- Blood clots. Blood clots in the arteries, veins, brain, and lungs have happened in people with beta thalassemia during treatment with REBLOZYL. The risk of blood clots may be higher in people who have had their spleen removed or who take hormone replacement therapy or birth control (oral contraceptives). Call your healthcare provider or get medical help right away if you get any of these symptoms:
  - chest pain
  - trouble breathing or shortness of breath
  - pain in your leg, with or without swelling
  - a cold or pale arm or leg
  - sudden numbness or weakness that are both short-term or continue to happen over a long period of time, especially on one side of the body
  - severe headache or confusion
  - sudden problems with vision, speech, or balance (such as trouble speaking, difficulty walking, or dizziness)
- High blood pressure. REBLOZYL may cause an increase in your blood pressure. Your healthcare provider will check your blood pressure before you receive your REBLOZYL dose. Your healthcare provider may prescribe you medicine to treat high blood pressure or increase the dose of medicine you already take to treat high blood pressure if you develop high blood pressure during treatment with REBLOZYL.
- Extramedullary Hematopoietic (EMH) Masses. EMH masses have happened in people with beta thalassemia during treatment with REBLOZYL. You may have a higher risk for developing EMH masses if you have a history of EMH masses, have had your spleen removed, have or have had an enlarged spleen or liver, or have low hemoglobin levels. Your healthcare provider will monitor you before you start and during treatment with REBLOZYL. Call your healthcare provider or get medical help right away if you get any of these symptoms:
  - severe pain in the back
  - numbness, weakness, or loss of voluntary movement in feet, legs, hands, or arms
  - loss of bowel and bladder control

The most common side effects of REBLOZYL include:

- tiredness
- headache
- back, joint, muscle, or bone pain
- joint pain
- dizziness
- nausea
- diarrhea

- cough
- stomach (abdominal) pain
- trouble breathing
- swelling of your hands, legs, or feet
- high blood pressure
- allergic reactions

REBLOZYL may cause fertility problems in females. This could affect your ability to become pregnant. Talk to your healthcare provider if this is a concern for you.
These are not all of the possible side effects of REBLOZYL.
Call your doctor for medical advice about side effects. You may report side effects to FDA at 1-800-FDA-1088.

General information about the safe and effective use of REBLOZYL.
Medicines are sometimes prescribed for purposes other than those listed in a Patient Information leaflet. You can ask your healthcare provider or pharmacist for information about REBLOZYL that is written for health professionals.

What are the ingredients in REBLOZYL?
Active ingredient: luspatercept-aamt
Inactive ingredients: citric acid monohydrate, polysorbate 80, sucrose, and tri-sodium citrate dihydrate.

For more information, go to www.REBLOZYL.com or call 1-888-423-5436.

Manufactured by: Celgene Corporation, a Bristol-Myers Squibb Company, 86 Morris Avenue, Summit, NJ 07901

REBLOZYL® is a registered trademark of Celgene Corporation, a Bristol-Myers Squibb Company.

REBPPI V5 8/2023

This Patient Information has been approved by the U.S. Food and Drug Administration

Revised: August 2023

PRINCIPAL DISPLAY PANEL - 25 mg Vial Label

NDC 59572-711-01

Reblozyl®
(luspatercept-aamt)
for Injection

25 mg/vial

For Subcutaneous Use Only
Reconstitute prior
to administration

LOT
EXP

PRINCIPAL DISPLAY PANEL - 25 mg Vial Carton - USA

NDC 59572-711-01
Rx only

Reblozyl®
(luspatercept-aamt)
for Injection

25 mg/vial

For Subcutaneous Use Only
Reconstitute with Sterile Water
for Injection USP, prior to
administration.

One Single-Dose Vial
Discard Unused Portion

PRINCIPAL DISPLAY PANEL - 25 mg Vial Carton - Singapore

NDC 59572-711-01
Rx only

Reblozyl®
(luspatercept-aamt)
for Injection

25 mg/vial

For Subcutaneous Use Only
Reconstitute with Sterile Water
for Injection USP, prior to
administration.

One Single-Dose Vial
Discard Unused Portion

PRINCIPAL DISPLAY PANEL - 75 mg Vial Label

NDC 59572-775-01

Reblozyl®
(luspatercept-aamt)
for Injection

75 mg/vial

For Subcutaneous Use Only
Reconstitute prior
to administration

LOT
EXP

PRINCIPAL DISPLAY PANEL - 75 mg Vial Carton - USA

NDC 59572-775-01
Rx only

Reblozyl®
(luspatercept-aamt)
for Injection

75 mg/vial

For Subcutaneous Use Only
Reconstitute with Sterile Water
for Injection USP, prior to
administration.

One Single-Dose Vial
Discard Unused Portion

PRINCIPAL DISPLAY PANEL - 75 mg Vial Carton - Singapore

NDC 59572-775-01
Rx only

Reblozyl®
(luspatercept-aamt)
for Injection

75 mg/vial

For Subcutaneous Use Only
Reconstitute with Sterile Water
for Injection USP, prior to
administration.

One Single-Dose Vial
Discard Unused Portion